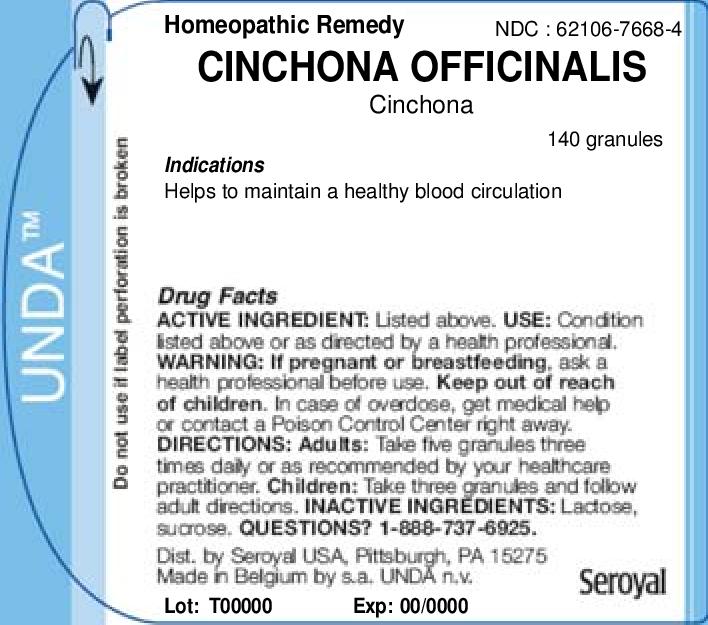 DRUG LABEL: CINCHONA OFFICINALIS
NDC: 62106-7668 | Form: GRANULE
Manufacturer: Seroyal USA
Category: homeopathic | Type: HUMAN OTC DRUG LABEL
Date: 20221109

ACTIVE INGREDIENTS: CINCHONA OFFICINALIS BARK 2 [hp_X]/1 1
INACTIVE INGREDIENTS: LACTOSE; SUCROSE

CINCHONA OFFICINALIS

Active Ingredients

CINCHONA OFFICINALIS 12CH GR

CINCHONA OFFICINALIS 15CH GR

CINCHONA OFFICINALIS 200K GR

CINCHONA OFFICINALIS 30CH GR

CINCHONA OFFICINALIS 30K GR

CINCHONA OFFICINALIS 4CH GR

CINCHONA OFFICINALIS 5CH GR

CINCHONA OFFICINALIS 7CH GR

CINCHONA OFFICINALIS 9CH GR

PURPOSE

Indications

Helps to maintain a healthy blood circulation

Warning:
If pregnant or breastfeeding, ask a health professional before use.
Keep out of reach of children.
In case of overdose, get medical help or contact a Poison Control Center right away.

PREGNANCY OR BREAST FEEDING

If pregnant or breastfeeding, ask a health professional before use.

Keep out of reach of children.

OVERDOSAGE

In case of overdose, get medical help or contact a Poison Control Center right away.

Inactive Ingredients
Lactose,
sucrose.

Directions
Adults: Take five granules three times daily or as recommended by your healthcare practitioner.
Children: Take three granules and follow adult directions.

QUESTIONS? 1-888-737-6925.

Indications

Helps to maintain a healthy blood circulation

Directions
Adults: Take five granules three times daily or as recommended by your healthcare practitioner.
Children: Take three granules and follow adult directions.

PACKAGE LABEL

UNDA
Do not use if label perforation is broken
Homeopathic Remedy
NDC : 62106-7668-4
CINCHONA OFFICINALIS
Cinchona
140 granules
Indications

Helps to maintain a healthy blood circulation